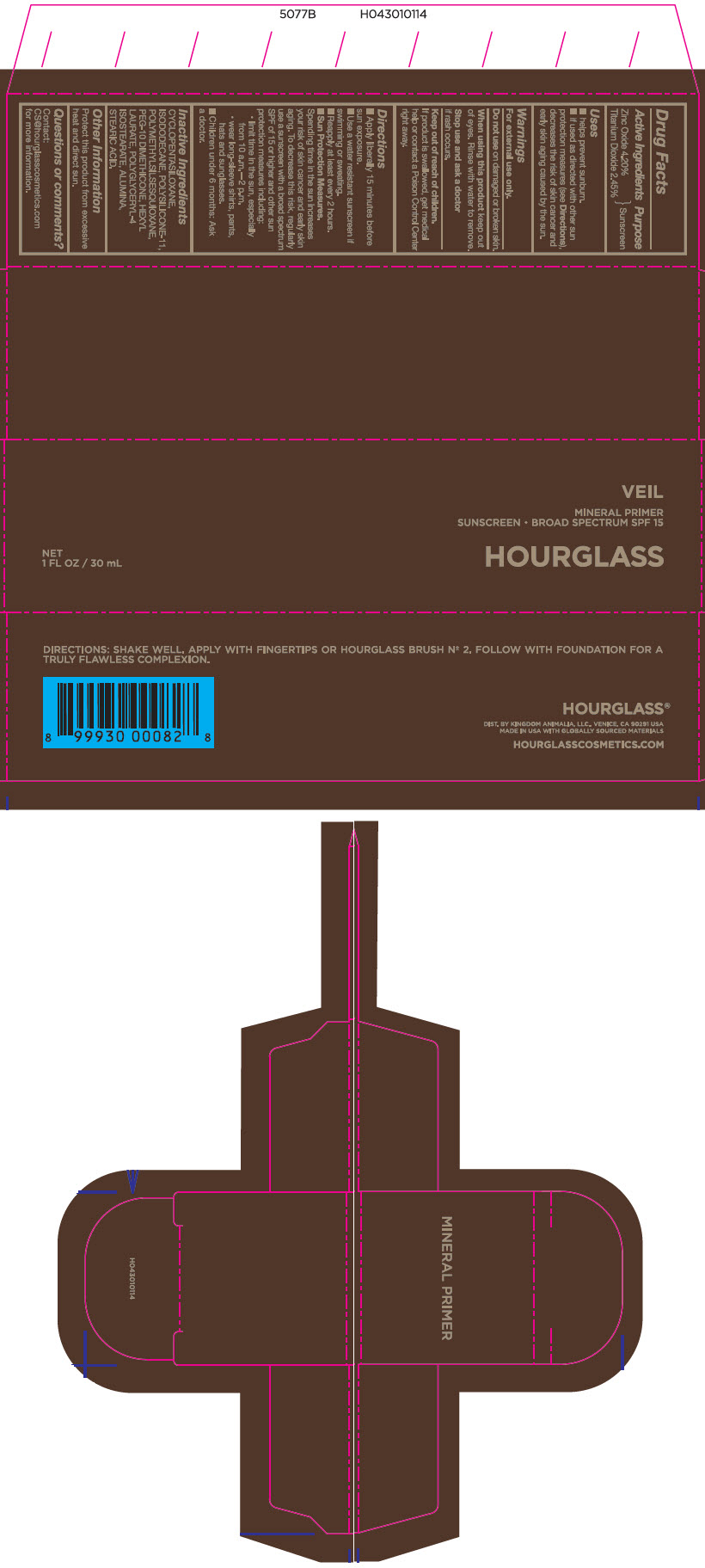 DRUG LABEL: VEIL MINERAL PRIMER SUNSCREEN BROAD SPECTRUM SPF 15
NDC: 42627-101 | Form: LOTION
Manufacturer: Kingdom Animalia, LLC DBA Hourglass Cosmetics
Category: otc | Type: HUMAN OTC DRUG LABEL
Date: 20251124

ACTIVE INGREDIENTS: ZINC OXIDE 4.2 g/100 mL; TITANIUM DIOXIDE 2.45 g/100 mL
INACTIVE INGREDIENTS: CYCLOMETHICONE 5; ISODODECANE; DIMETHICONE/VINYL DIMETHICONE CROSSPOLYMER (SOFT PARTICLE); POLYMETHYLSILSESQUIOXANE (4.5 MICRONS); PEG-10 DIMETHICONE (600 CST); HEXYL LAURATE; POLYGLYCERYL-4 ISOSTEARATE; ALUMINUM OXIDE; STEARIC ACID

VEIL MINERAL PRIMER SUNSCREEN BROAD SPECTRUM SPF 15

Drug Facts

Active Ingredients

Zinc Oxide 4.20%

Titanium Dioxide 2.45%

Purpose

Sunscreen

Uses

- helps prevent sunburn.
- if used as directed with other sun protection measures (see Directions), decreases the risk of skin cancer and early skin aging caused by the sun.

Warnings

For external use only.

Do not use on damaged or broken skin.

When using this product keep out of eyes. Rinse with water to remove.

Stop use and ask a doctor if rash occurs.

Keep out of reach of children. If product is swallowed, get medical help or contact a Poison Control Center right away.

Directions

- Apply liberally 15 minutes before sun exposure.
- Use a water resistant sunscreen if swimming or sweating.
- Reapply at least every 2 hours.
- Sun Protection Measures. Spending time in the sun increases your risk of skin cancer and early skin aging. To decrease this risk, regularly use a sunscreen with a broad spectrum SPF of 15 or higher and other sun protection measures including:
  - limit time in the sun, especially from 10 a.m.—2 p.m.
  - wear long-sleeve shirts, pants, hats and sunglasses.
- Children under 6 months: Ask a doctor.

Inactive Ingredients

CYCLOPENTASILOXANE, ISODODECANE, POLYSILICONE-11, POLYMETHYLSILSES-QUIOXANE, PEG-10 DIMETHICONE, HEXYL LAURATE, POLYGLYCERYL-4 ISOSTEARATE, ALUMINA, STEARIC ACID

Other Information

Protect this product from excessive heat and direct sun.

Questions or comments?

Contact:

CS@hourglasscosmetics.com for more information.

PRINCIPAL DISPLAY PANEL - 30 mL Bottle Carton

VEIL

MINERAL PRIMER
SUNSCREEN • BROAD SPECTRUM SPF 15

HOURGLASS

NET
1 FL OZ / 30 mL